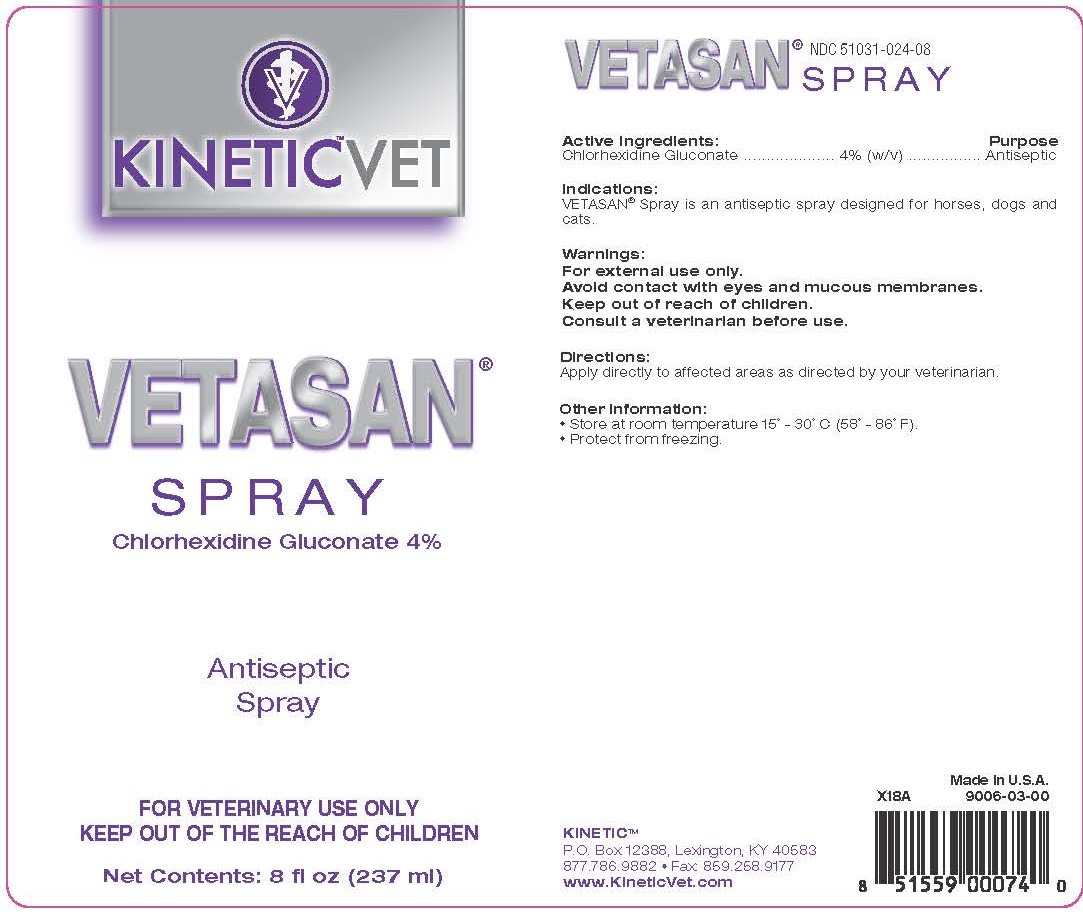 DRUG LABEL: Vetasan
NDC: 51031-024 | Form: SPRAY
Manufacturer: Kinetic Technologies, LLC
Category: animal | Type: OTC ANIMAL DRUG LABEL
Date: 20231127

ACTIVE INGREDIENTS: CHLORHEXIDINE GLUCONATE 4 g/100 mL

Vetasan Spray

Active Ingredients:

Chlorhexidine Gluconate.........4% (w/v)

Purpose

Antiseptic

Indications:

VETASAN® Spray is an antiseptic spray designed for horses, dogs and cats.

Warnings:

For external use only.

Avoid contact with eyes and mucous membranes.

Keep out of reach of children.

Consult a veterinarian before use.

Directions:

Apply directly to affected areas as directed by your veterinarian.

Other Information:

- Store at room temperature 15° - 30°C (58° - 86°F).
- Protect from freezing.

KINETIC™

P.O. Box 12388, Lexington KY 40583

877.786.9882 • Fax: 859.258.9177

www.KineticVet.com

Made in U.S.A.

#9006-03-00

KINETIC™VET

VETASAN® SPRAY

Chlorhexidine Gluconate 4%

Antiseptic Spray

FOR VETERINARY USE ONLY

KEEP OUT OF THE REACH OF CHILDREN

Net Contents: 8 fl oz (237 ml)